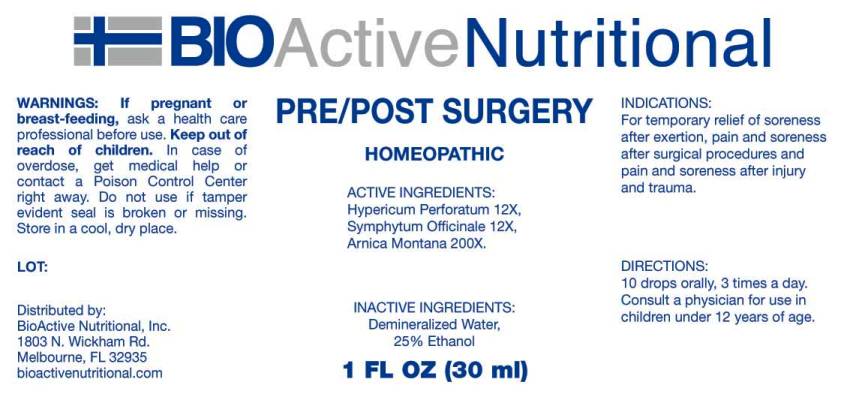 DRUG LABEL: Pre Post Surgery
NDC: 43857-0061 | Form: LIQUID
Manufacturer: BioActive Nutritional, Inc.
Category: homeopathic | Type: HUMAN OTC DRUG LABEL
Date: 20161110

ACTIVE INGREDIENTS: HYPERICUM PERFORATUM 12 [hp_X]/1 mL; COMFREY ROOT 12 [hp_X]/1 mL; ARNICA MONTANA 200 [hp_X]/1 mL
INACTIVE INGREDIENTS: WATER; ALCOHOL

Drug Facts:

ACTIVE INGREDIENTS:

Hypericum Perforatum 12X, Symphytum Officinale 12X, Arnica Montana 200X.

INDICATIONS:

For temporary relief of soreness after exertion, pain and soreness after surgical procedures and pain and soreness after injury and trauma.

WARNINGS:

If pregnant or breast-feeding, ask a health care professional before use.

Keep out of reach of children. In case of overdose, get medical help or contact a Poison Control Center right away.

Do not use if tamper evident seal is broken or missing.

Store in cool, dry place.

DIRECTIONS:

10 drops orally, 3 times a day. Consult a physician for use in children under 12 years of age.

INACTIVE INGREDIENTS:

Demineralized Water, 25% Ethanol.

Keep out of reach of children. In case of overdose, get medical help or contact a Poison Control Center right away.

INDICATIONS:

For temporary relief of soreness after exertion, pain and soreness after surgical procedures and pain and soreness after injury and trauma.

QUESTIONS:

Distributed by:
BioActive Nutritional, Inc.
1803 N. Wickham Rd.
Melbourne, FL 32935
bioactivenutritional.com

PACKAGE LABEL DISPLAY:

BIOActive Nutritional

PRE POST SURGERY

HOMEOPATHIC

1 FL OZ (30 ml)